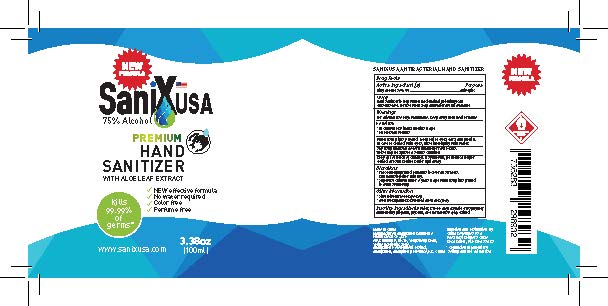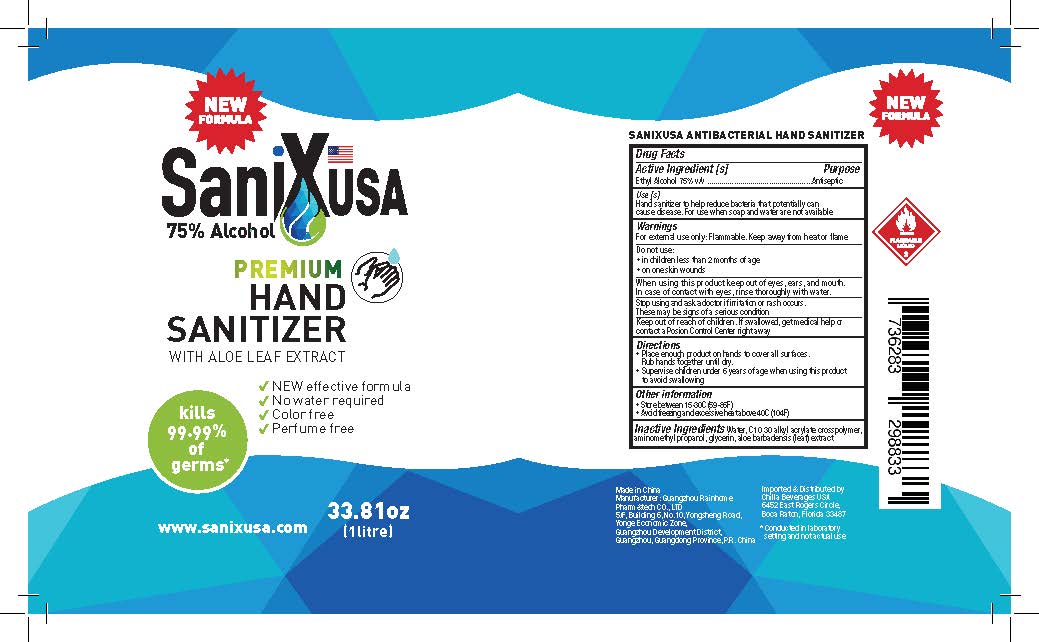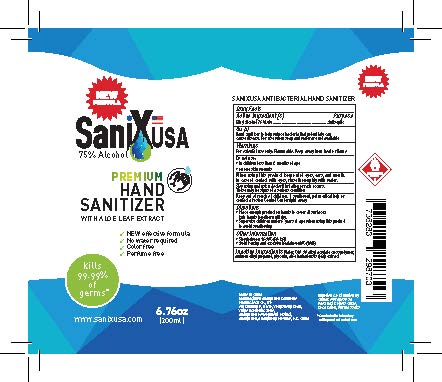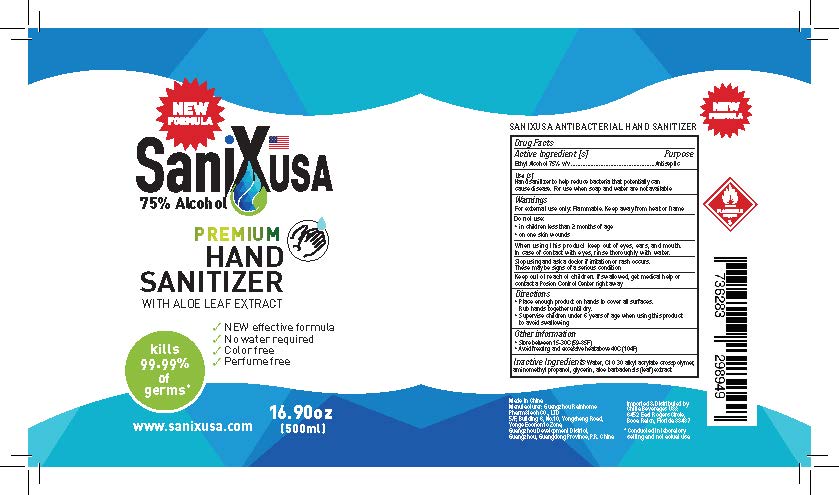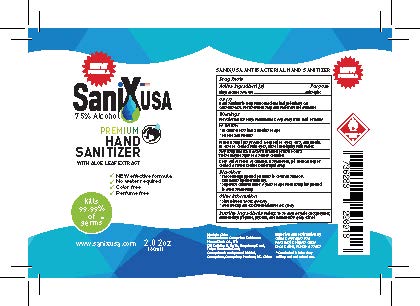 DRUG LABEL: Sanixusa  Hand Sanitizer
NDC: 78126-110 | Form: GEL
Manufacturer: GUANGZHOU RAINHOME PHARM&TECH CO., LTD
Category: otc | Type: HUMAN OTC DRUG LABEL
Date: 20200526

ACTIVE INGREDIENTS: ALCOHOL 75 mL/100 mL
INACTIVE INGREDIENTS: WATER; ALOE VERA LEAF; AMINOMETHYLPROPANOL; CARBOMER COPOLYMER TYPE A (ALLYL PENTAERYTHRITOL CROSSLINKED); GLYCERIN

Sanixusa Hand Sanitizer

Active Ingredient

Ethyl Alcohol 75%

Purpose

Antiseptic

Uses

Hand Sanitizer to help reduce bacteria that potentially can cause disease. For use when soap and water are not available

Warnings

For External Use Only. FLAMMABLE. Keep away from heat or flame.

Do not use

In children less than 2 months of age. On open skin wounds.

When using this product

Keep out of eyes, ears, and mouth. In case of contact with eyes, rinse eyes thoroughly with water.

Stop use and ask a doctor.

If irritation or rash occurs. These may be signs of a serious condition.

Keep out of reach of children.

If swallowed, get medical help or contact a Poison Control Center right away.

Directions

Place enough product on hands to cover all surfaces. Rub hands together until dry. Supervise children under 6 years of age when using this product to avoid swallowing

Other Information

Store between 15-30C (59-85F).

Avoid freezing and excessive heat above 40C (104F)

Inactive Ingredients

Water, C10 30 alkyl acrylate crosspolymer, aminomethyl propanol, glycerin, aloe barbadensis (leaf) extract